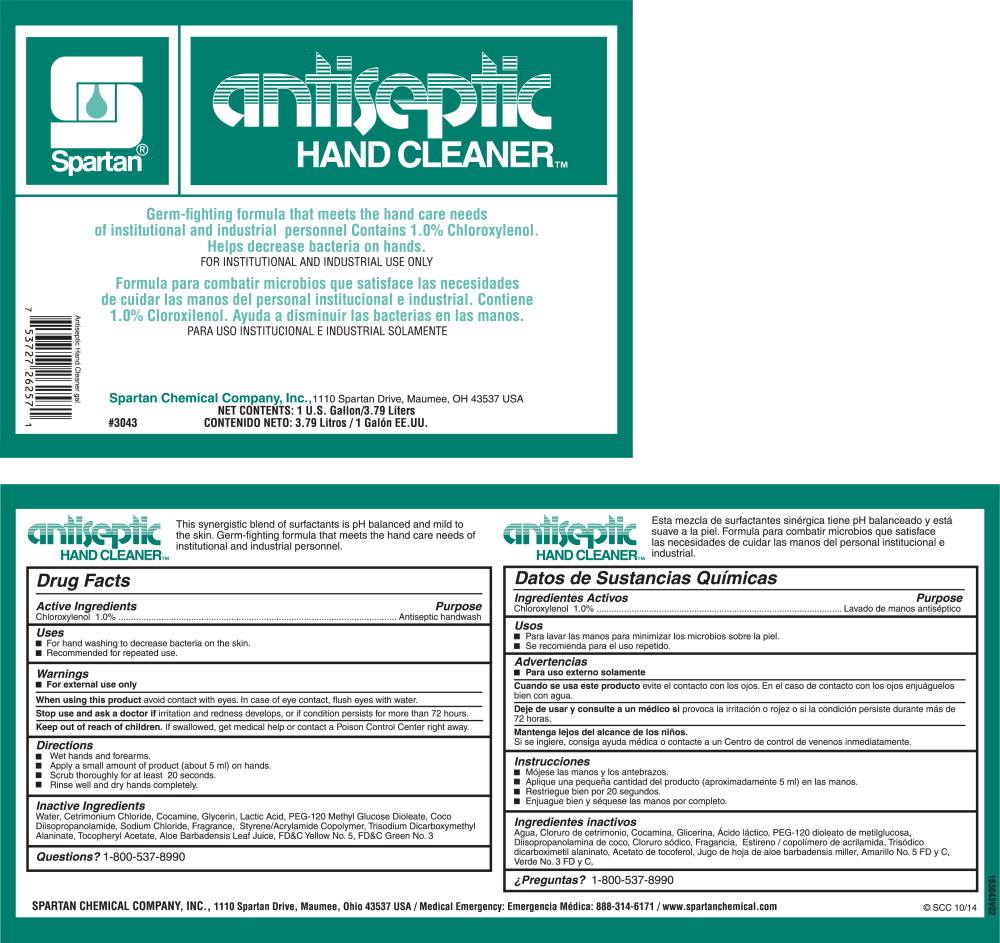 DRUG LABEL: Antiseptic Hand Cleaner
NDC: 64009-336 | Form: SOAP
Manufacturer: Spartan Chemical Company, Inc.
Category: otc | Type: HUMAN OTC DRUG LABEL
Date: 20251006

ACTIVE INGREDIENTS: CHLOROXYLENOL 10.11 g/1 L
INACTIVE INGREDIENTS: WATER; CETRIMONIUM CHLORIDE; COCAMINE; GLYCERIN; LACTIC ACID, L-; PEG-120 METHYL GLUCOSE DIOLEATE; COCO DIISOPROPANOLAMIDE; SODIUM CHLORIDE; TRISODIUM DICARBOXYMETHYL ALANINATE, L-; .ALPHA.-TOCOPHEROL ACETATE; ALOE VERA LEAF; FD&C YELLOW NO. 5; FD&C GREEN NO. 3

Drug Facts

Active Ingredients

Chloroxylenol 1.0%

Purpose

Antiseptic handwash

Uses

- For hand washing to decrease bacteria on the skin.
- Recommended for repeated use.

Warnings

- For external use only

When using this product avoid contact with eyes. In case of eye contact, flush eyes with water.

Stop use and ask doctor if irritation and redness develops, or if condition persists for more than 72 hours.

Keep out of reach of children. If swallowed, get medical help or contact a Poison Control Center right away.

Directions

- Wet hands and forearms.
- Apply a small amount of product (about 5 ml) on hands.
- Scrub thoroughly for at least 20 seconds.
- Rinse well and dry hands completely.

Inactive Ingredients

Water, Cetrimonium Chloride, Cocamine, Glycerin, Lactic Acid, PEG-120 Methyl Glucose Dioleate, Coco Diisopropanolamide, Sodium Chloride, Fragrance, Styrene/Acrylamide Copolymer, Trisodium Dicarboxymethyl Alaninate, Tocopheryl Acetate, Aloe Barbadensis Leaf Juice, FD&C Yellow No. 5, FD&C Green No. 3

Questions?

1-800-537-8990

Principal Display Panel - 3.79 Liters Container Label

Spartan®

ANTISEPTIC

HAND CLEANERTM

Germ-fighting formula that meets the hand care needs
of institutional and industrial personnel Contains 1.0% Chloroxylenol.

Helps decrease bacteria on hands.

FOR INSTITUTIONAL AND INDUSTRIAL USE ONLY

Formula para combatir microbios que satisface las necesidades
de cuidar las manos del personal institucional e industrial. Contiene
1.0% Cloroxilenol. Ayuda a disminuir las bacterias en las manos.

PARA USO INSTITUCIONAL E INDUSTRIAL SOLAMENTE

Spartan Chemical Company, Inc., 1110 Spartan Drive, Maumee, OH 43537 USA

NET CONTENTS: 1 U.S. Gallon/3.79 Liters

CONTENIDO NETO: 3.79 Litros / 1 Galon EE.UU.

#3043